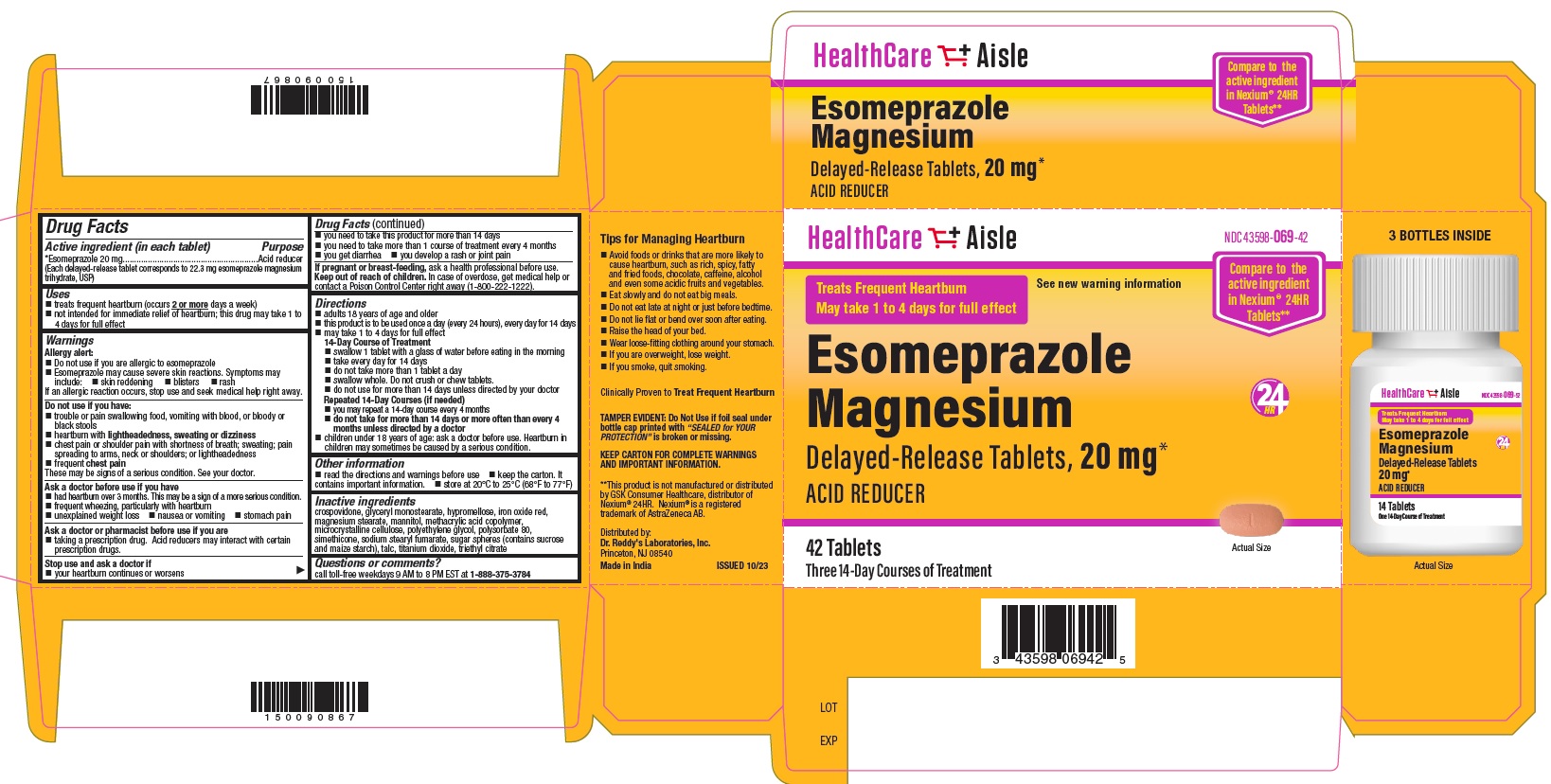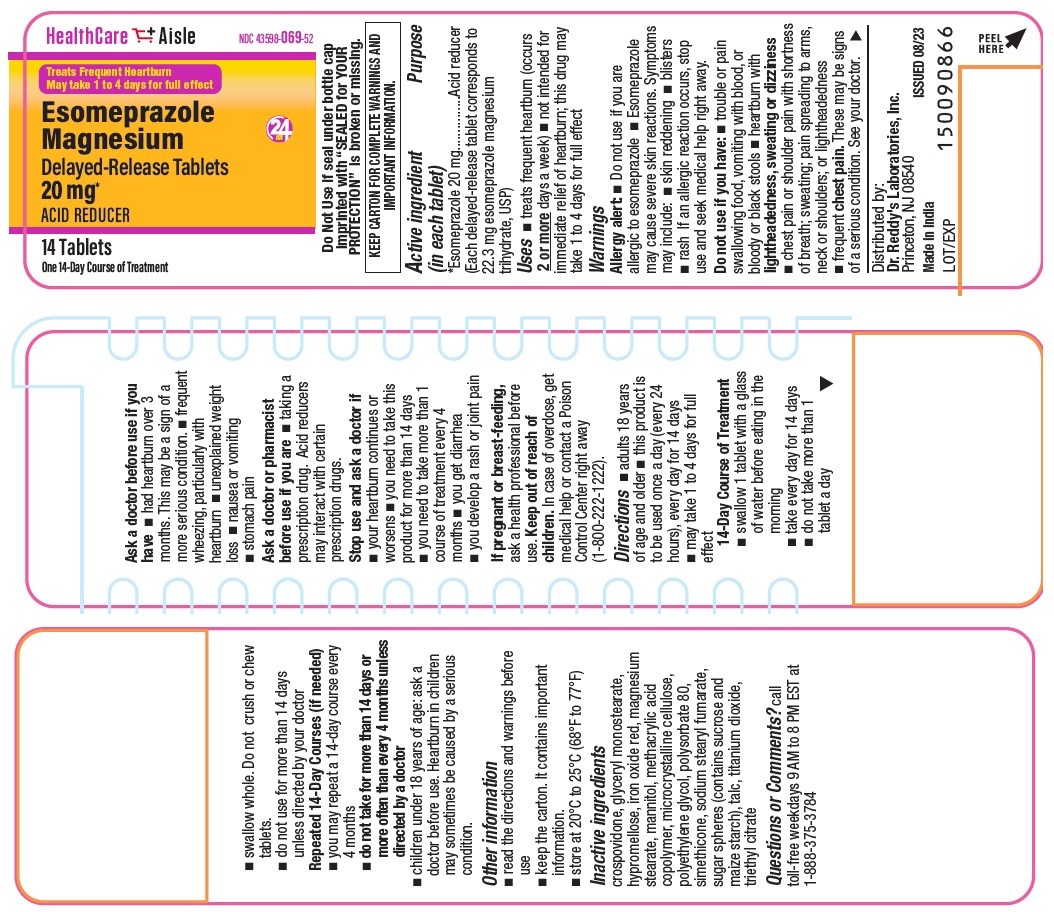 DRUG LABEL: Esomeprazole Magnesium
NDC: 43598-069 | Form: TABLET, DELAYED RELEASE
Manufacturer: Dr. Reddys Laboratories Inc
Category: otc | Type: HUMAN OTC DRUG LABEL
Date: 20251104

ACTIVE INGREDIENTS: Esomeprazole Magnesium 20 mg/1 1
INACTIVE INGREDIENTS: Crospovidone; Glyceryl Monostearate; Hypromelloses; Ferric Oxide Red; Magnesium Stearate; Mannitol; METHACRYLIC ACID AND ETHYL ACRYLATE COPOLYMER; Cellulose, Microcrystalline; Polyethylene Glycol, Unspecified; Polysorbate 80; Dimethicone 350; Sodium Stearyl Fumarate; Sucrose; Talc; Titanium Dioxide; Triethyl Citrate

Drug Facts

Active ingredient(in each tablet)

*Esomeprazole 20 mg

(Each delayed-release tablet corresponds to 22.3 mg esomeprazole magnesium trihydrate, USP)

Purpose

Acid reducer

Uses

- treats frequent heartburn (occurs 2 or more days a week)
- not intended for immediate relief of heartburn; this drug may take 1 to 4 days for full effect

Warnings

Allergy alert:

- Do not use if you are allergic to esomeprazole
- Esomeprazole may cause severe skin reactions.

Symptoms may include:

- skin reddening
- blisters
- rash

If an allergic reaction occurs, stop use and seek medical help right away.

Do not use if you have:

- trouble or pain swallowing food, vomiting with blood, or bloody or black stools
- heartburn with lightheadedness, sweating or dizziness·
- chest pain or shoulder pain with shortness of breath; sweating; pain spreading to arms, neck or shoulders; or lightheadness·
- frequent chest pain

These may be signs of a serious condition. See your doctor.

Ask a doctor before use if you have

- had heartburn over 3 months. This may be a sign of a more serious condition.·
- frequent wheezing, particularly with heartburn·
- unexplained weight loss·
- nausea or vomiting·
- stomach pain

Ask a doctor or pharmacist before use if you are

- taking a prescription drug. Acid reducers may interact with certain prescription drugs.

Stop use and ask a doctor if

- your heartburn continues or worsens
- you need to take this product for more than 14 days·
- you need to take more than 1 course of treatment every 4 months·
- you get diarrhea·
- you develop a rash or joint pain

Pregnancy/Breastfeeding

If pregnant or breast-feeding, ask a health professional before use.

Keep out of reach of children. In case of overdose, get medical help or contact a Poison Control Center right away (1-800-222-1222).

Directions

- adults 18 years of age and older·
- this product is to be used once a day (every 24 hours), every day for 14 days·
- may take 1 to 4 days for full effect

14-Day Course of Treatment

- swallow 1 tablet with a glass of water before eating in the morning·
- take every day for 14 days
- do not take more than 1 tablet a day
- swallow whole. Do not crush or chew tablets
- do not use for more than 14 days unless directed by your doctor

Repeated 14-Day Courses (if needed)

- you may repeat a 14-day course every 4 months·
- do not take for more than 14 days or more often than every 4 months unless directed by a doctor
- children under 18 years of age, ask a doctor before use. Heartburn in children may sometimes be caused by a serious condition.

Other information

- read directions and warnings before use·
- keep the carton. It contains important information

Storage

- store at 20°C to 25°C (68°F to 77°F)

Inactive ingredients

crospovidone, glyceryl monostearate, hypromellose, iron oxide red, magnesium stearate, mannitol, methacrylic acid copolymer, microcrystalline cellulose, polyethylene glycol, polysorbate 80, simethicone, sodium stearyl fumarate, sugar spheres (contains sucrose and maize starch), talc, titanium dioxide, triethyl citrate

Questions or comments?

call toll-free weekdays 9 AM to 8 PM EST at 1-888-375-3784

Tips for Managing Heartbun

- Avoid foods or drinks that are more likely to cause heartburn, such as rich, spicy, fatty and fried foods, chDistocolate, caffeine, alcohol and even some acidic fruits and vegetables
- Eat slowly and do not eat big meals.
- Do not eat late at night or just before bedtime
- Do not lie flat or bend over soon after eating
- Raise the head of your bed.
- Wear loose-fitting clothing around your stomach
- If you are overweight, lose weight
- If you smoke, quit smoking.

Distributor:

Dr. Reddy’s Laboratories Inc.,

Princeton, NJ 08540

Made in India

Issued: 10/2023

Principal Display Panel

Container label 14count:

PACKAGE LABEL

Carton 14's count: